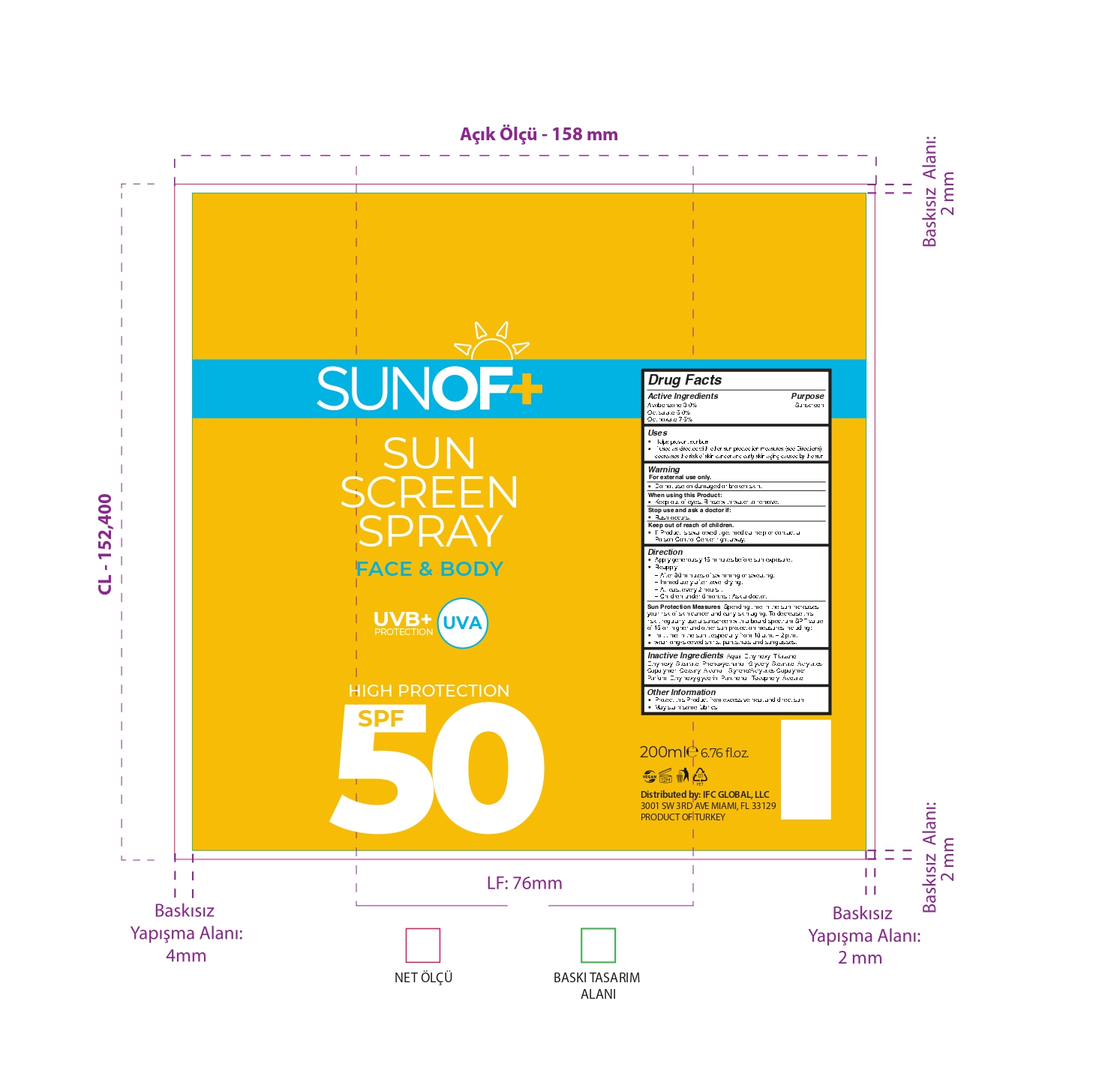 DRUG LABEL: SUNOF Sunscreen SPF 50
NDC: 77418-002 | Form: SPRAY
Manufacturer: ATAK FARMA KOZMETIK VE KIMYA SANAYI TICARET ANONIM SIRKETI
Category: otc | Type: HUMAN OTC DRUG LABEL
Date: 20250812

ACTIVE INGREDIENTS: AVOBENZONE 3 g/100 mL; OCTINOXATE 7.5 g/100 mL; OCTISALATE 5 g/100 mL
INACTIVE INGREDIENTS: ETHYLHEXYL TRIAZONE; PHENOXYETHANOL; AQUA; PANTHENOL; ETHYLHEXYLGLYCERIN; PARFUMIDINE; ETHYLHEXYL STEARATE; GLYCERYL STEARATE; ACRYLATES CROSSPOLYMER-4; CETEARYL ALCOHOL

Inactive Ingredients

Aqua , Ethylhexyl Triazone ,

Ethylhexyl Stearate , Phenoxyethanol , Glyceryl Stearate , Acrylates Copolymer , Cetearyl Alcohol , Styrene/Acrylates Copolymer , Parfum , Ethylhexylglycerin ,Panthenol ,Tocopheryl Acetate.

Warnings

For external use only.

Do not use on damaged or broken skin.

When using this Product

Keep out of eyes.Rinse with water to remove.

Stop use and ask a doctor if rash occurs.

Active Ingredients

Avobenzone 3.0%

Octisalate 5.0%

Octinoxate 7.5%

Other Warnings

Protect this Product from excessive heat and direct sun

May stain some fabrics

Keep out of reach of children

If Product is swallowed , get medical help or contact a Poison Control Center right away.

Directions

Apply generously 15 minutes before sun exposure. reapply : after 80 minutes of swimming or sweating.Immediately after towel drying. At least every 2 hours . Children under 6 months : Ask a doctor. Sun Protection Measures . Spending time in the sun increases your risk of skin cancer and early skin aging. To decrease this risk , regularly use a sunscreen with a board spectrum SPF value of 15 or higher and other sun protection measures including: limit time in the sun , especially from 10 a.m. – 2 p.m. wear long-sleeved shirts, pants,hats and sunglasses.

USES

Helps prevent sunburn

If used as directed with other sun proctection measures (see Directions), decreases the risk of skin cancer and early skin aging caused by the sun.

Purpose

Helps prevent sunburn